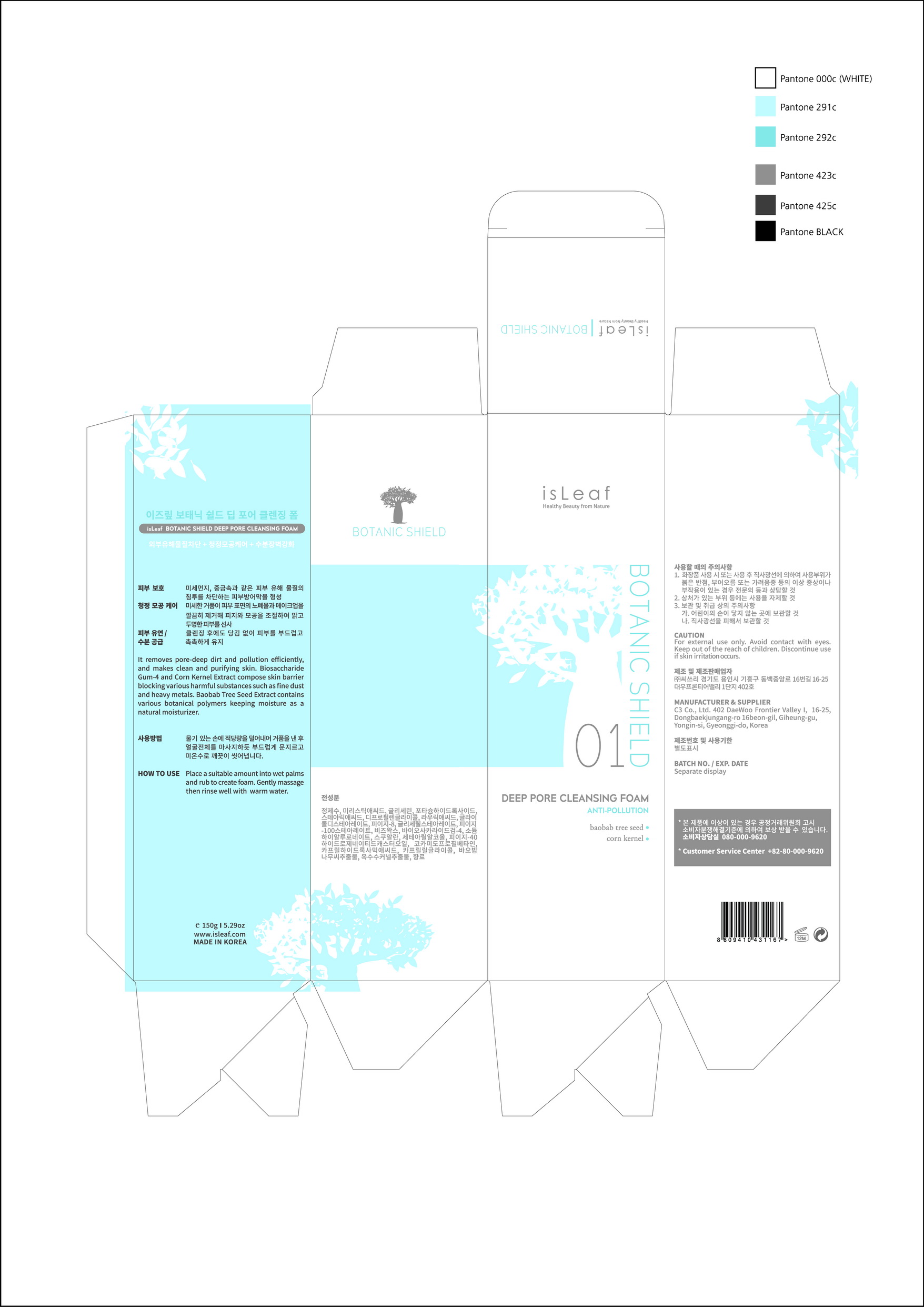 DRUG LABEL: isLeaf Botanic Shield Deep Pore Cleasing Foam
NDC: 70818-015 | Form: LIQUID
Manufacturer: C3 Co., Ltd.
Category: otc | Type: HUMAN OTC DRUG LABEL
Date: 20170828

ACTIVE INGREDIENTS: GLYCERIN 11 g/100 g
INACTIVE INGREDIENTS: WATER

Drug Facts

ACTIVE INGREDIENT

glycerin

INACTIVE INGREDIENT

water, squalane, beeswax, etc.

PURPOSE

skin protectant

keep out of reach of the children

INDICATIONS AND USAGE

Place a suitable amount into wet palms and rub to create foam. Gently massage then rinse well with warm water

WARNINGS

1. If the following symptoms occur after product use, stop using the product immediately and consult a dermatologist (continuous use can exacerbate the symptoms).
1) Occurrence of red spots, swelling, itchiness, and other skin irritation
2) If the symptoms above occur after the application area is exposed to direct sunlight
2. Do not use on open wounds, eczema, and other skin irritations
3. Precaution for Storage and Handling
1) Close the lid after use
2) Keep out of reach of infants and children
3) Do not to store in a place with high/low temperature and exposed to direct sunlight

4. Use as avoiding eye areas.

DOSAGE AND ADMINISTRATION

for external use only